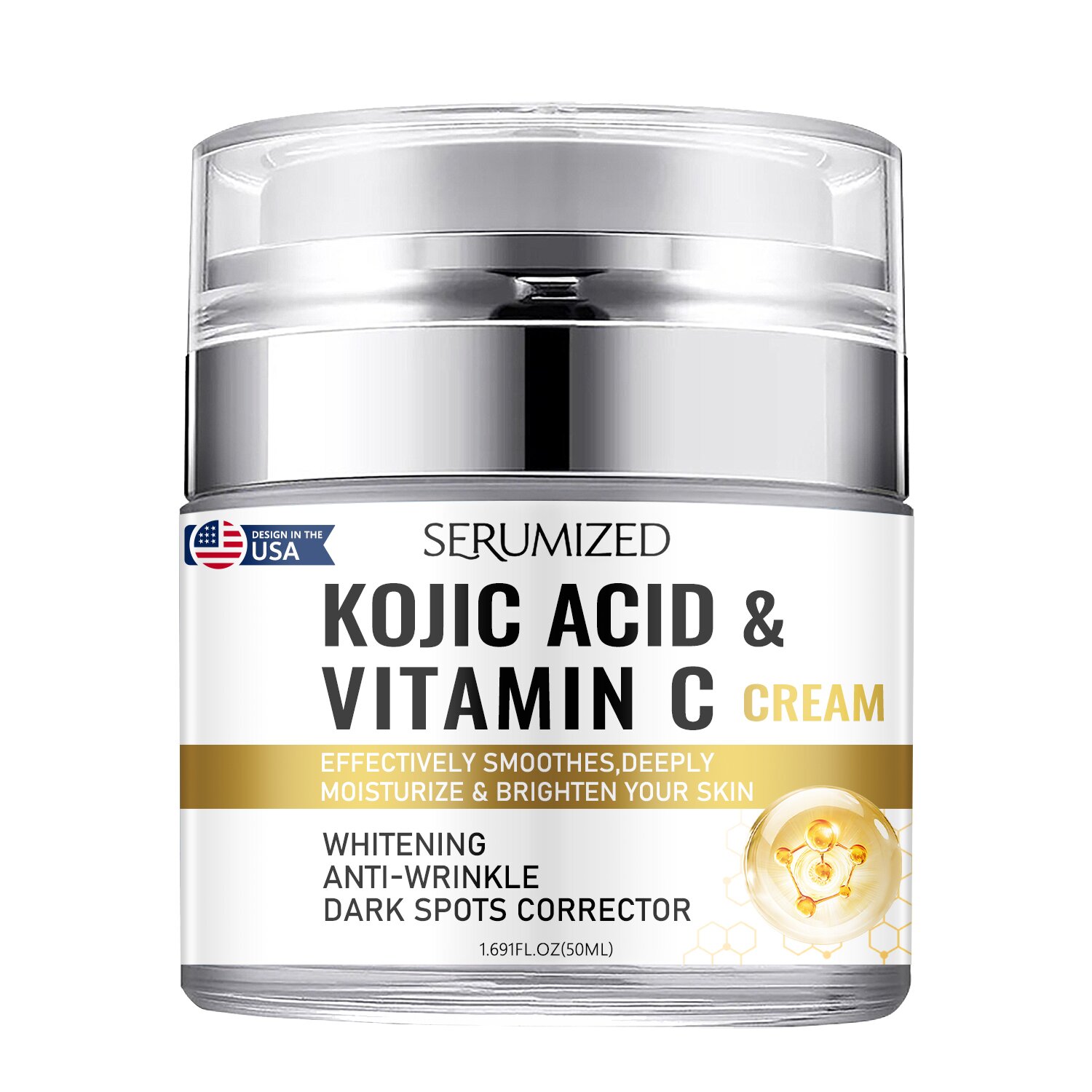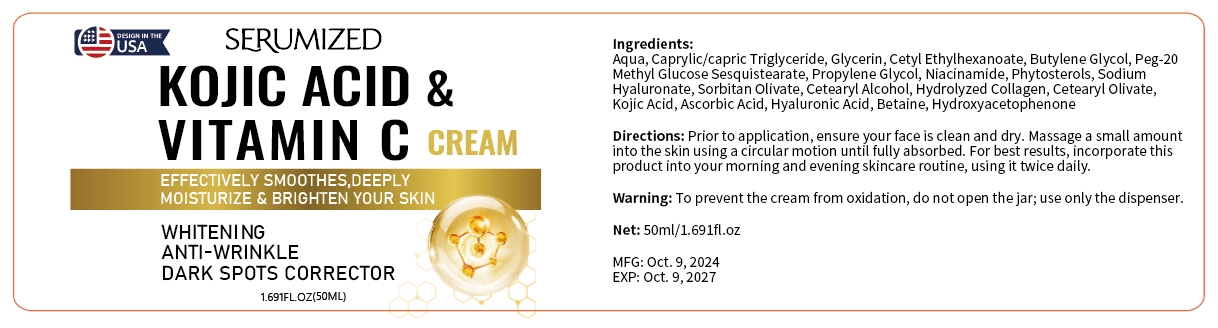 DRUG LABEL: kojic acid vitamin c cream
NDC: 84025-288 | Form: CREAM
Manufacturer: Guangzhou Yanxi Biotechnology Co., Ltd
Category: otc | Type: HUMAN OTC DRUG LABEL
Date: 20241220

ACTIVE INGREDIENTS: CAPRYLIC/CAPRIC TRIGLYCERIDE 5 mg/100 mL; GLYCERIN 3 mg/100 mL
INACTIVE INGREDIENTS: WATER

DOSAGE AND ADMINISTRATION

Prior to application, ensure your face is clean and dry. Massage a small amountinto the skin using a circular motion until fully absorbed. For best results, incorporate thisproduct into your morning and evening skincare routine, using it twice daily.

WARNINGS

Keep out of children

INACTIVE INGREDIENT

Aqua

INDICATIONS AND USAGE

for daily face care

keep out of children

PURPOSE

Firm and hydrate the face